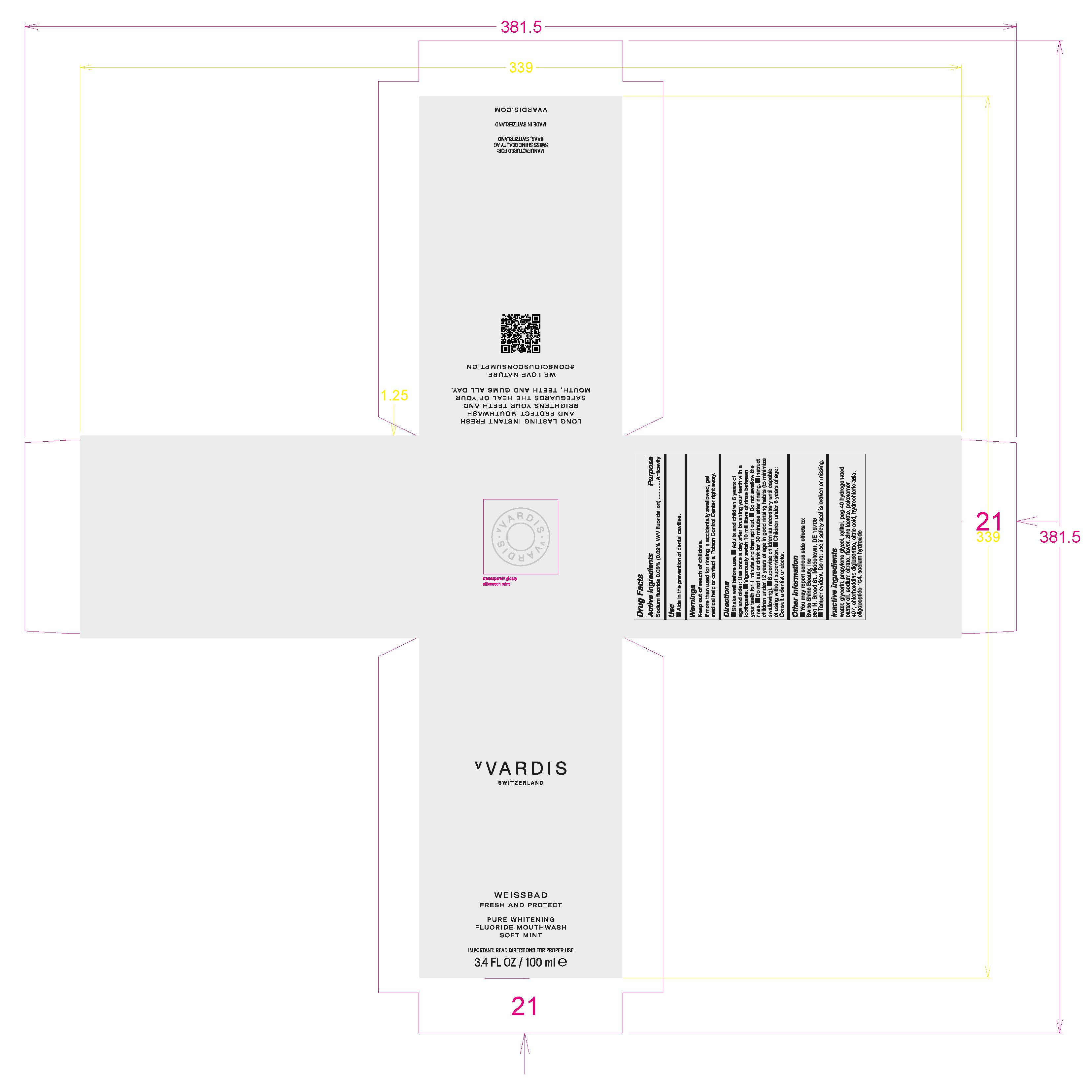 DRUG LABEL: Fluoride Mouthwash Soft Mint
NDC: 79763-002 | Form: MOUTHWASH
Manufacturer: Swiss Shine Beauty AG
Category: otc | Type: HUMAN OTC DRUG LABEL
Date: 20200803

ACTIVE INGREDIENTS: SODIUM FLUORIDE 0.05 g/100 mL
INACTIVE INGREDIENTS: SODIUM CITRATE; SODIUM HYDROXIDE; CITRIC ACID MONOHYDRATE; ZINC LACTATE; POLOXAMER 407; CHLORHEXIDINE GLUCONATE; PROPYLENE GLYCOL; POLYOXYL 40 HYDROGENATED CASTOR OIL; WATER; XYLITOL; HYDROCHLORIC ACID; GLYCERIN

Fluoride Mouthwash Soft Mint

Active Ingredients

Sodium fluoride 0.05% (0.02% w/v fluoride ion) Purpose: Anticavity

Use

- Aids in the prevention of dental cavities.

Keep out of reach of children.

If more than used for rinsing is accidently swallowed, get medical help or contact a Poison Control Center right away.

INDICATIONS AND USAGE

Do not swallow the rinse

Keep out of reach of children.

If more than used for rinsing is accidently swallowed, get medical help or contact a Poison Control Center right away.

Directions

- Shake well before use.
- Adults and children 6 years of age and older: Use once a day after brushing yout teeth with a toothpaste.
- Vigorously swish 10 milliliters of rinse between your teeth for 1 minute and then spit out.
- Do not swallow the rinse.
- Do not eat or drink for 30 minutes after rinsing.
- Instruct children under 12 years of age in good rinsing habits (to minimize swallowing).
- Supervise children as necessary until capable of using without supervision.
- Children under 6 years of age: Consult a dentist or doctor.

OTHER SAFETY INFORMATION

- You may report serious side effects to: Swiss Shine Beauty, Inc

651 N. Broad St., Middletown, DE 19709

- Tamper evident: Do not use if safety seal is broken or missing.

Inactive ingredients

water, glycerin, propylene glycol, xylitol, peg-40 hydrogenated castor oil, sodium citrate, flavor, zinc lactate, poloxamer 407, chlorhexidine digluconate, citric acid, hydrochloric acid, oligopeptide-104, sodium hydroxide

PACKAGE LABEL

vVARDIS

SWITZERLAND

WEISSBAD

FRESH AND PROTECT

PURE WHITENING

FLUORIDE MOUTHWASH

SOFT MINT

IMPORTANT: READ DIRECTIONS FOR PROPER USE

3.4 FL OZ / 100 ml e